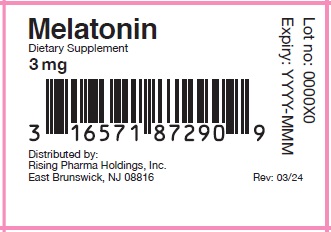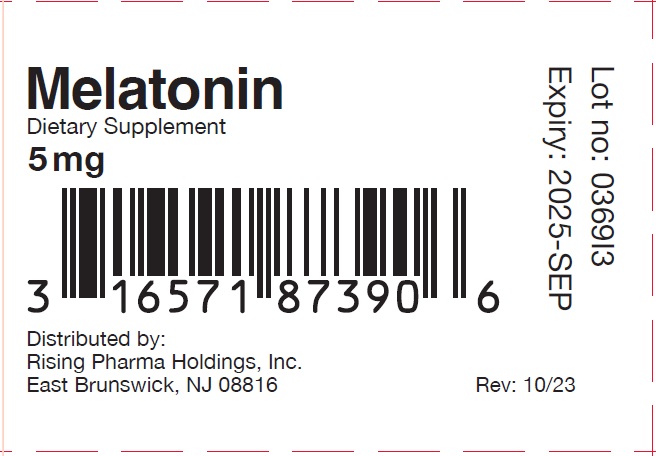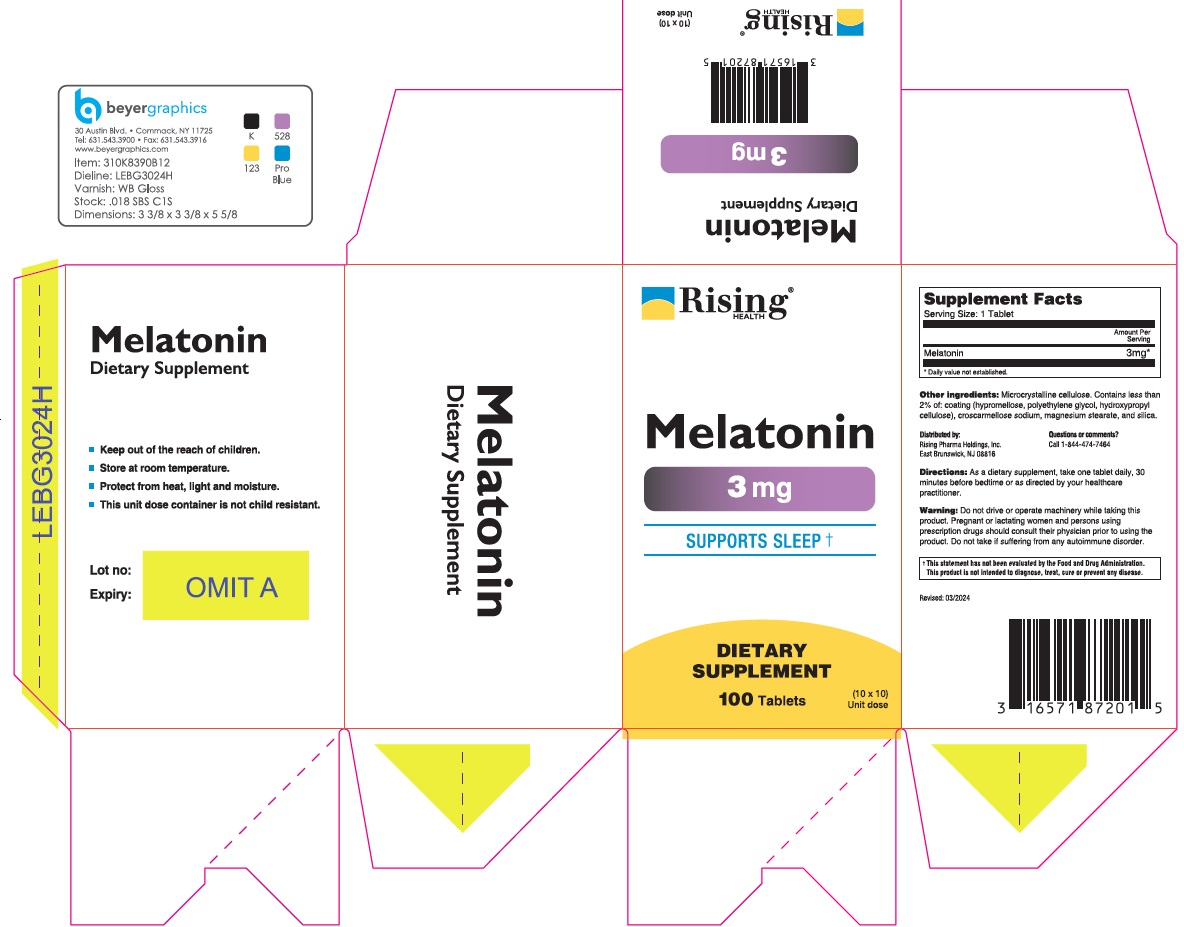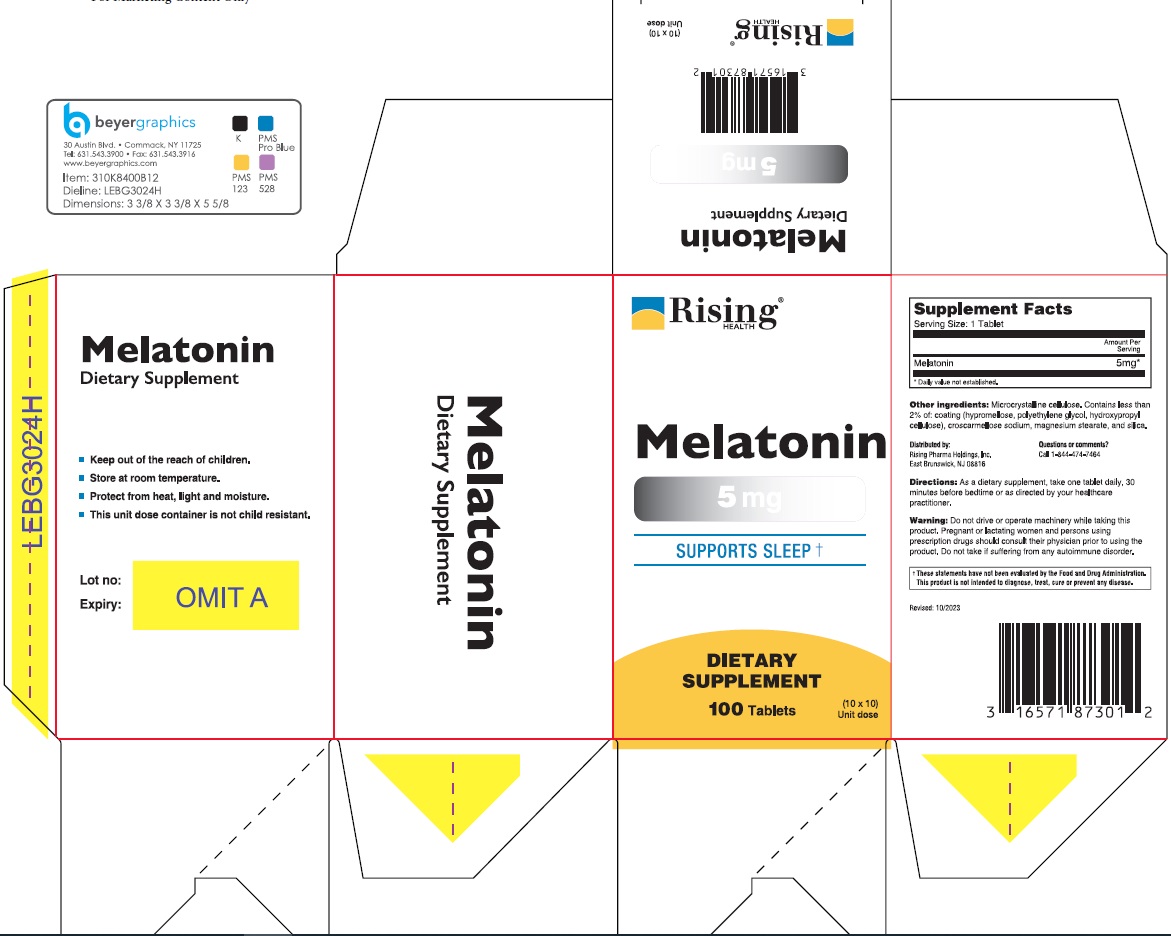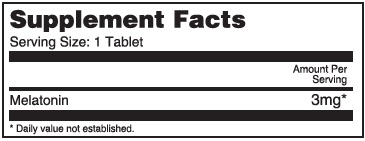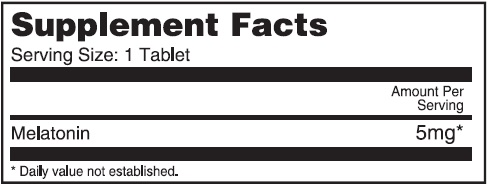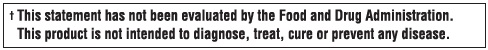 DRUG LABEL: Melatonin
NDC: 16571-872 | Form: TABLET
Manufacturer: Rising Pharma Holdings, Inc.
Category: other | Type: DIETARY SUPPLEMENT
Date: 20250623

ACTIVE INGREDIENTS: Melatonin 3 mg/1 1
INACTIVE INGREDIENTS: MICROCRYSTALLINE CELLULOSE; HYPROMELLOSE, UNSPECIFIED; POLYETHYLENE GLYCOL, UNSPECIFIED; HYDROXYPROPYL CELLULOSE, UNSPECIFIED; CROSCARMELLOSE SODIUM; MAGNESIUM STEARATE; SILICON DIOXIDE

Melatonin Tablets, 3 mg and 5 mg
Dietary Supplement
100 Tablets (10x10) Unit dose

STATEMENT OF IDENTITY

Supplement Facts - 3 mg

Supplement Facts - 5 mg

HEALTH CLAIM

Other ingredients: Microcrystalline cellulose. Contains less than 2% of: coating (hypromellose, polyethylene glycol, hydroxypropyl cellulose), croscarmellose sodium, magnesium stearate, and silica.

DOSAGE AND ADMINISTRATION

Directions: As a dietary supplement, take one tablet daily, 30 minutes before bedtime or as directed by your healthcare practitioner.

WARNINGS

Warning: Do not drive or operate machinery while taking this product. Pregnant or lactating women and persons using prescription drugs should consult their physician prior to using the product. Do not take if suffering from any autoimmune disorder.

SAFE HANDLING WARNING

- Keep out of the reach of children.
- Store at room temperature.
- Protect from heat, light and moisture.
- This unit dose container is not child resistant.

Questions or comments?

Call 1-844-474-7464

Distributed by:
Rising Pharma Holdings, Inc.
East Brunswick, NJ 08816

3mg - Revised: 03/2024

5mg - Revised: 10/2023

PRINCIPAL DISPLAY PANEL

Melatonin - 3 mg

Dietary Supplement

100 Tablets (10x10) Unit dose

Blister label (16571-872-90)

Carton label (16571-872-01)

Melatonin - 5 mg

Dietary Supplement

100 Tablets (10x10) Unit dose

Blister label (16571-873-90)

Carton label (16571-873-01)